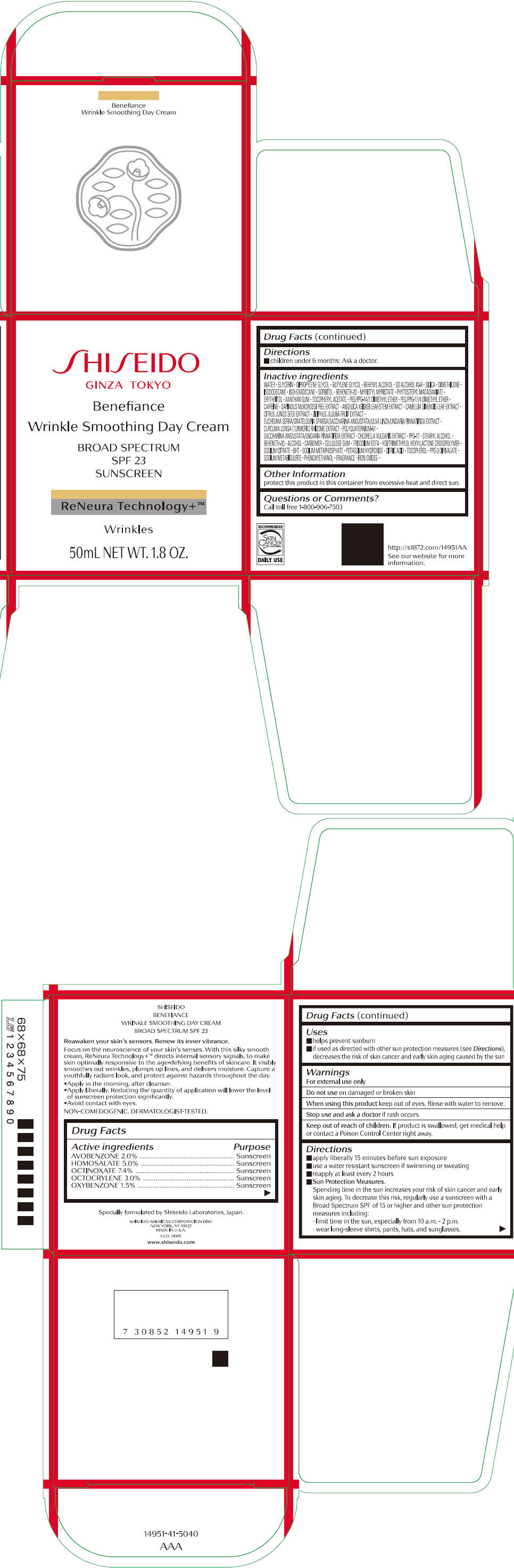 DRUG LABEL: SHISEIDO BENEFIANCE WRINKLE SMOOTHING DAY
NDC: 58411-439 | Form: CREAM
Manufacturer: SHISEIDO AMERICAS CORPORATION
Category: otc | Type: HUMAN OTC DRUG LABEL
Date: 20260105

ACTIVE INGREDIENTS: AVOBENZONE 1032 mg/50 mL; HOMOSALATE 2580 mg/50 mL; OCTINOXATE 3818 mg/50 mL; OCTOCRYLENE 1548 mg/50 mL; OXYBENZONE 774 mg/50 mL
INACTIVE INGREDIENTS: WATER; GLYCERIN; DIPROPYLENE GLYCOL; BUTYLENE GLYCOL; DOCOSANOL; SILICON DIOXIDE; DIMETHICONE; ISODODECANE; ISOHEXADECANE; SORBITOL; BEHENETH-20; MYRISTYL MYRISTATE; ERYTHRITOL; XANTHAN GUM; .ALPHA.-TOCOPHEROL ACETATE, DL-; PEG/PPG-14/7 DIMETHYL ETHER; PEG/PPG-17/4 DIMETHYL ETHER; CAFFEINE; SAPINDUS MUKOROSSI FRUIT RIND; ANGELICA KEISKEI TOP; GREEN TEA LEAF; CITRUS JUNOS SEED; JUJUBE FRUIT; TURMERIC; POLYQUATERNIUM-51 (2-METHACRYLOYLOXYETHYL PHOSPHORYLCHOLINE/N-BUTYL METHACRYLATE; 3:7); CHLORELLA VULGARIS; PPG-17; STEARYL ALCOHOL; BEHENETH-30; ALCOHOL; CARBOMER HOMOPOLYMER, UNSPECIFIED TYPE; CARBOXYMETHYLCELLULOSE SODIUM, UNSPECIFIED; EDETATE TRISODIUM; HEXAMETHYLENE DIISOCYANATE/TRIMETHYLOL HEXYLLACTONE CROSSPOLYMER; SODIUM CITRATE, UNSPECIFIED FORM; BUTYLATED HYDROXYTOLUENE; SODIUM POLYMETAPHOSPHATE; POTASSIUM HYDROXIDE; CITRIC ACID MONOHYDRATE; .ALPHA.-TOCOPHEROL; SODIUM METABISULFITE; PHENOXYETHANOL; FERRIC OXIDE RED; FERRIC OXIDE YELLOW; FERROSOFERRIC OXIDE

SHISEIDO BENEFIANCE WRINKLE SMOOTHING DAY CREAM

Drug Facts

ACTIVE INGREDIENT

Active ingredients | Purpose
AVOBENZONE 2.0% | Sunscreen
HOMOSALATE 5.0% | Sunscreen
OCTINOXATE 7.4% | Sunscreen
OCTOCRYLENE 3.0% | Sunscreen
OXYBENZONE 1.5% | Sunscreen

Uses

- helps prevent sunburn
- if used as directed with other sun protection measures (see Directions), decreases the risk of skin cancer and early skin aging caused by the sun

Warnings

For external use only

Do not useon damaged or broken skin

WHEN USING

When using this productkeep out of eyes. Rinse with water to remove.

Stop use and ask a doctorif rash occurs

Keep out of reach of children.If product is swallowed, get medical help or contact a Poison Control Center right away.

Directions

For sunscreen use:

- apply liberally 15 minutes before sun exposure
- use a water resistant sunscreen if swimming or sweating
- reapply at least every 2 hours
- Sun Protection Measures. Spending time in the sun increases your risk of skin cancer and early skin aging. To decrease this risk, regularly use a sunscreen with a broad spectrum SPF of 15 or higher and other sun protection measures including:
  - limit time in the sun, especially from 10 a.m. – 2 p.m.
  - wear long-sleeve shirts, pants, hats, and sunglasses
- children under 6 months: Ask a doctor

Inactive Ingredients

WATER•GLYCERIN•DIPROPYLENE GLYCOL•BUTYLENE GLYCOL•BEHENYL ALCOHOL•SD ALCOHOL 40-B•SILICA•DIMETHICONE•ISODODECANE•ISOHEXADECANE•SORBITOL•BEHENETH-20•MYRISTYL MYRISTATE•PHYTOSTERYL MACADAMIATE•ERYTHRITOL•XANTHAN GUM•TOCOPHERYL ACETATE•PEG/PPG-14/7 DIMETHYL ETHER•PEG/PPG-17/4 DIMETHYL ETHER•CAFFEINE•SAPINDUS MUKOROSSI PEEL EXTRACT•ANGELICA KEISKEI LEAF/STEM EXTRACT•CAMELLIA SINENSIS LEAF EXTRACT•CITRUS JUNOS SEED EXTRACT•ZIZIPHUS JUJUBA FRUIT EXTRACT•EUCHEUMA SERRA/GRATELOUPIA SPARSA/SACCHARINA ANGUSTATA/ULVA LINZA/UNDARIA PINNATIFIDA EXTRACT•CURCUMA LONGA (TURMERIC) RHIZOME EXTRACT•POLYQUATERNIUM-51•SACCHARINA ANGUSTATA/UNDARIA PINNATIFIDA EXTRACT•CHLORELLA VULGARIS EXTRACT•PPG-17•STEARYL ALCOHOL•BEHENETH-30•ALCOHOL•CARBOMER•CELLULOSE GUM•TRISODIUM EDTA•HDI/TRIMETHYLOL HEXYLLACTONE CROSSPOLYMER•SODIUM CITRATE•BHT•SODIUM METAPHOSPHATE•POTASSIUM HYDROXIDE•CITRIC ACID•TOCOPHEROL•PPG-3 DIPIVALATE•SODIUM METABISULFITE•PHENOXYETHANOL•FRAGRANCE•IRON OXIDES•

Other information

- protect this product in this container from excessive heat and direct sun.

Questions or comments?

Call toll free 1-800-906-7503

PRINCIPAL DISPLAY PANEL - 50 mL Jar Carton

SHISEIDO
GINZA TOKYO

Benefiance

Wrinkle Smoothing Day Cream

BROAD SPECTRUM
SPF 23
SUNSCREEN

ReNeura Technology+™

Wrinkles

50mL NET WT. 1.8 OZ.